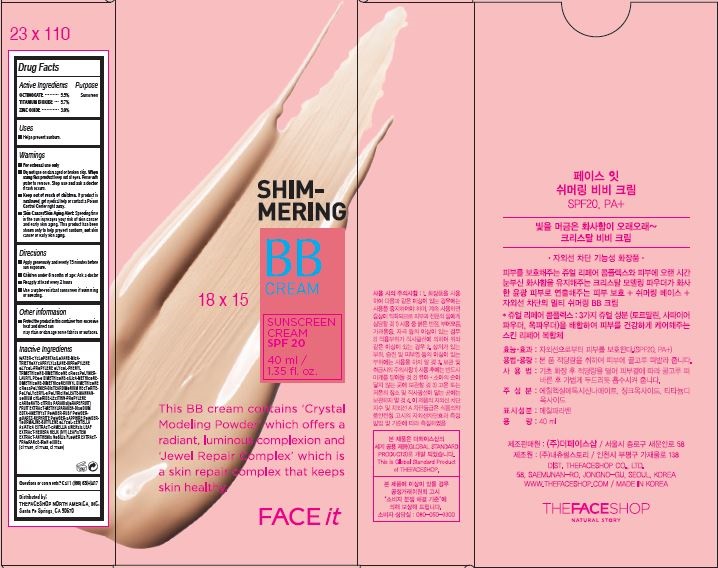 DRUG LABEL: FACE IT
NDC: 51523-285 | Form: CREAM
Manufacturer: THEFACESHOP NORTH AMERICA, INC.
Category: otc | Type: HUMAN OTC DRUG LABEL
Date: 20141120

ACTIVE INGREDIENTS: OCTINOXATE 2.2 g/40 mL; TITANIUM DIOXIDE 2.28 g/40 mL; ZINC OXIDE 1.2 g/40 mL
INACTIVE INGREDIENTS: WATER

Active Ingredients

OCTINOXATE.......... .5.5%

TITANIUM DIOXIDE .5.7%

ZINC OXIDE ............. 3.0%

Purpose

Sunscreen
Sunscreen
Sunscreen

Uses

Helps prevent sunburn

Warnings

For external use only.

Do not use on damaged or broken skin.

When using this product keep out of eyes.

Rinse with water to remove.

Stop use and ask a doctor if rash occurs.

Keep out of reach of children.

If product is swallowed, get medical help or contact a Poison

Control Center right away.

Skin Cancer/Skin Aging Alert: Spending time

in the sun increases your risk of skin cancer

and early skin aging. This product has been

shown only to help prevent sunburn, not skin

cancer or early skin aging.

Directions

Apply generously and evenly 15 minutes before sun exposure.

Children under 6 months of age: Ask a doctor

Reapply at least every 2 hours.

Use a water-resistant sunscreen if swimming or sweating.

Other information

Protect the product in this container from excessive heat and direct sun.

May stain or damage some fabrics or surfaces.

Inactive Ingredients

WATER•CYCLOPENTASILOXANE•MICA•

TRIETHOXYCAPRYLYLSILANE•DIPROPYLENE

GLYCOL•PROPYLENE GLYCOL•PHENYL

TRIMETHICONE•DIMETHICONE CROSSPOLYMER•

LAURYL PEG-8 DIMETHICONE•SILICA•METHICONE•

DIMETHICONE•DIMETHICONE/VINYL DIMETHICONE

CROSSPOLYMER•DISTEARDIMONIUM HECTORITE•

POLYGLYCERYL-6 POLYRICINOLEATE•MANNAN•

SODIUM CHLORIDE•LECITHIN•PROPYLENE

CARBONATE•CITRUS PARADISI(GRAPEFRUIT)

FRUIT EXTRACT•METHYLPARABEN•DISODIUM

EDTA•AMETHYST POWDER•RUBY POWDER•

QUARTZ•NEPHRITE POWDER•SAPPHIRE POWDER•

TOURMALINE•BUTYLENE GLYCOL•CENTELLA

ASIATICA EXTRACT•CAMELLIA SINENSIS LEAF

EXTRACT•HEDERA HELIX (IVY) LEAF/STEM

EXTRACT•ANTHEMIS NOBILIS FLOWER EXTRACT•

FRAGRANCE•IRON OXIDES

(CI 77491, CI 77492, CI 77499)

Questions or comments?
Call 1 (866) 638-8417

Distributed by:

THEFACESHOP NORTH AMERICA, INC.

Santa Fe Springs, CA 90670

PACKAGE LABEL

SHIMMERING BB CREAM

SUNSCREEN CREAM SPF20

This BB cream contains "Crystal Modeling Powder" which offers a

radian, luminous complexion and "Jewel Repair Complex" which is

a skin repair complex that keeps skin healthy.